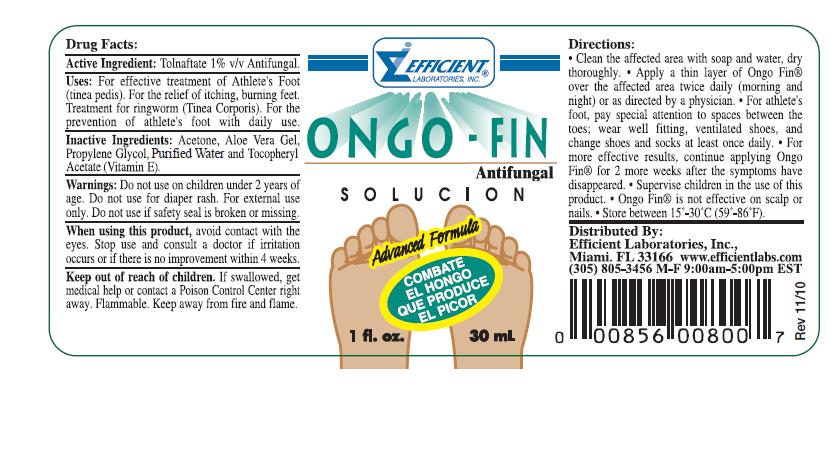 DRUG LABEL: Ongo - Fin
NDC: 58593-800 | Form: LIQUID
Manufacturer: Efficient Laboratories Inc.
Category: otc | Type: HUMAN OTC DRUG LABEL
Date: 20241014

ACTIVE INGREDIENTS: TOLNAFTATE 1 mg/100 mL
INACTIVE INGREDIENTS: ALOE VERA LEAF; PROPYLENE GLYCOL; WATER; ALPHA-TOCOPHEROL; ACETONE

Drud Facts

Active Ingredients:

Tolnaftate 1% v/v........Antifungal

Uses:

For effective treatment of Athlete's Foot (tinea pedis). For the relieve if itching, burning feet.

Treatment for ringworm (tinea corporis). For the prevention of athlete's foot with daily use.

Warnings:

Do not use on children under 2 years of age. Do not use for diaper rash. For external use only. Do not use if safety seal is broken or missing.

KEEP OUT OF REACH OF CHILDREN

Keep out of the reach of children. If swallowed, get medical help or contact a Poison Control Center right away. Flammable. Keep away from fire and flame.

Directions:

- Clean the affected area with soap and water, dry thoroughly.
- Apply a thin layer of Ongo Fin over the affected area twice daily (morning and night) or as directed by a physician.
- For athlete's foot, pay special attention to spaces between the toes; wear well fitting, ventilated shoes, and change shoes and socks at least once daily.
- For more effective results, continue applying Ongo Fin for 2 more weeks after the symptoms have disappeared.
- Supervise children in the use if this product.
- Ongo Fin is not effective on scalp or nails
- Store between 15 - 30 degrees celcius (59 - 86 degrees farhenheit).

When using this product, avoid contact with eyes. Stop use and consult a doctor if irritation occurs or if there is no improvement within 4 weeks.

Inactive Ingredients:

Acetone, Aloe Vera Gel, Propylene Glycol, Purified Water and Tocopheryl Acetate (Vitamin E).

QUESTIONS

Distributed By:

Effecient laboratories, Inc.
Miami FL 33166

www.efficientlab.com

(305) 805-3456 Monday to Friday

9:00am - 5:00pm EST